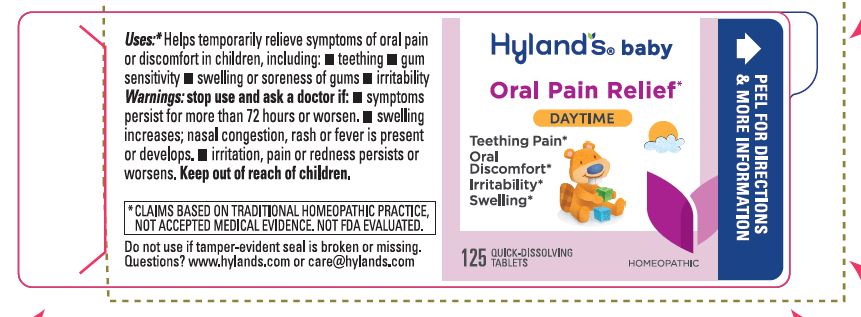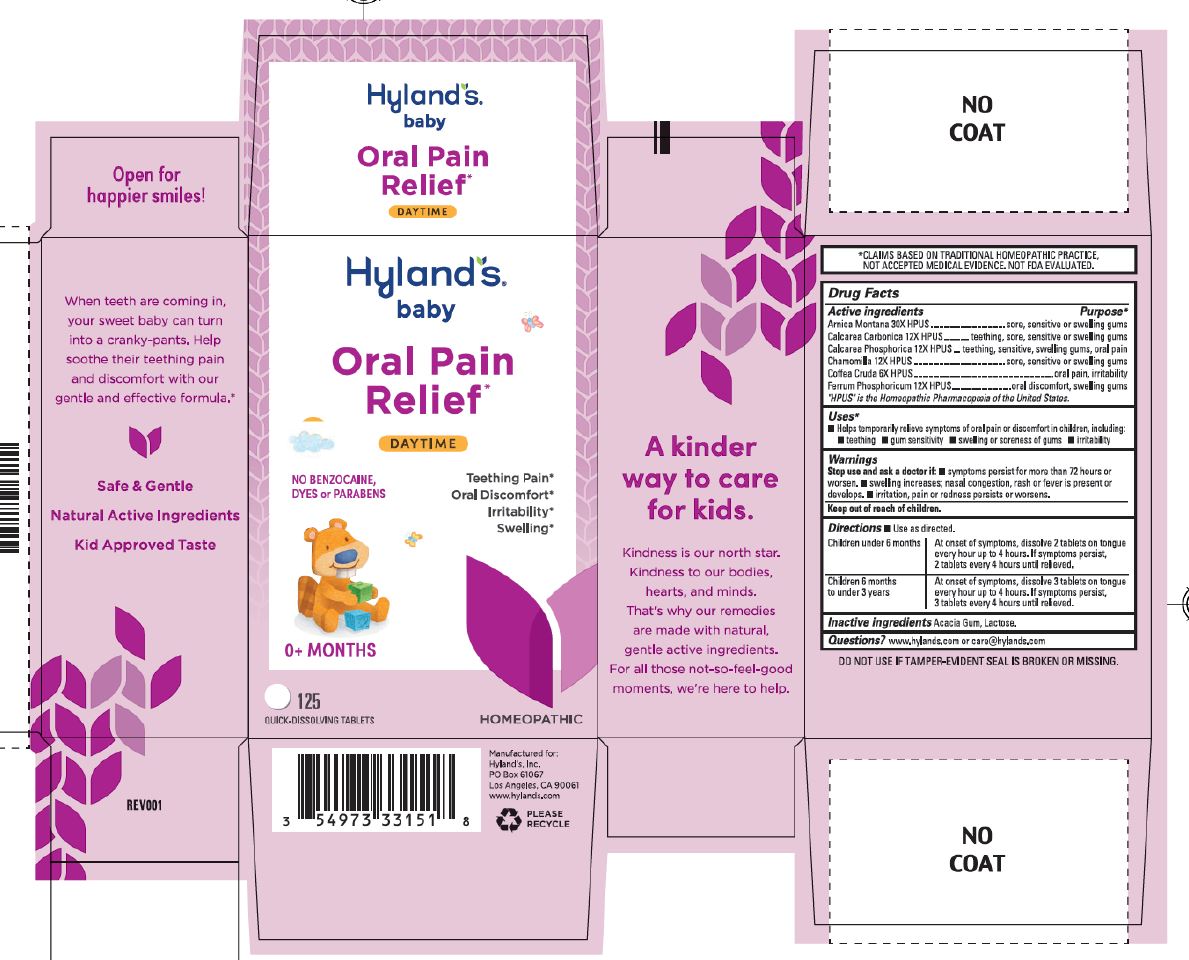 DRUG LABEL: Baby Oral Pain Relief
NDC: 54973-3315 | Form: TABLET
Manufacturer: Hyland' Inc.
Category: homeopathic | Type: HUMAN OTC DRUG LABEL
Date: 20250206

ACTIVE INGREDIENTS: OYSTER SHELL CALCIUM CARBONATE, CRUDE 12 [hp_X]/1 g; TRIBASIC CALCIUM PHOSPHATE 12 [hp_X]/1 g; ARABICA COFFEE BEAN 6 [hp_X]/1 g; ARNICA MONTANA 30 [hp_X]/1 g; MATRICARIA CHAMOMILLA 12 [hp_X]/1 g; FERRUM PHOSPHORICUM 12 [hp_X]/1 g
INACTIVE INGREDIENTS: ACACIA; LACTOSE MONOHYDRATE

Hyland's Naturals Baby Oral Pain Relief Daytime

Drug Facts

Active ingredients | Purpose
Arnica Montana 30X HPUS | sore, sensitive or swelling gums
Calcarea Carbonica 12X HPUS | teething, sore, sensitive or swelling gums
Calcarea Phosphorica 12X HPUS | teething, sensitive, swelling gums, oral pain
Chamomilla 12X HPUS | sore, sensitive or swelling gums
Coffea Cruda 6X HPUS | oral pain, irritability
Ferrum Phosphoricum 12X HPUS | oral discomfort, swelling gums

"HPUS" is the Homeopathic Pharmacopoeia of the United States.

Uses

■ Helps temporarily relieve symptoms of oral pain or discomfort in children, including:
■ teething ■ gum sensitivity ■ swelling or soreness of gums ■ irritability

Warnings

Stop use and ask a doctor if

■ symptoms persist for more than 72 hours or worsen. ■ swelling increases; nasal congestion, rash or fever is present or develops.

■ irritation, pain or redness persists or worsens.

Directions

■ Use as directed.

Children under 6 months | At onset of symptoms, dissolve 2 tablets on tongue every hour up to 4 hours. If symptoms persist, 2 tablets every 4 hours until relieved.
Children 6 months to under 3 years | At onset of symptoms, dissolve 3 tablets on tongue every hour up to 4 hours. If symptoms persist, 3 tablets every 4 hours until relieved.

Inactive ingredients

Acacia Gum, Lactose.

Questions?

www.hylands.com or care@hylands.com

PURPOSE

Helps temporarily relieve symptoms of oral pain or discomfort in children, including: teething, gum sensitivity, swelling or soreness of gums, irritability

Indications and Usage

Uses*

Removed *

Principal Display Panel

Hyland's

NATURALS™

•baby•

Oral Pain

Relief*

DAYTIME

NO BENZOCAINE,

DYES or PARABENS

Teething Pain
Oral Discomfort
Irritability
Swelling

0+ MONTHS

125

QUICK-DISSOLVING TABLETS

HOMEOPATHIC